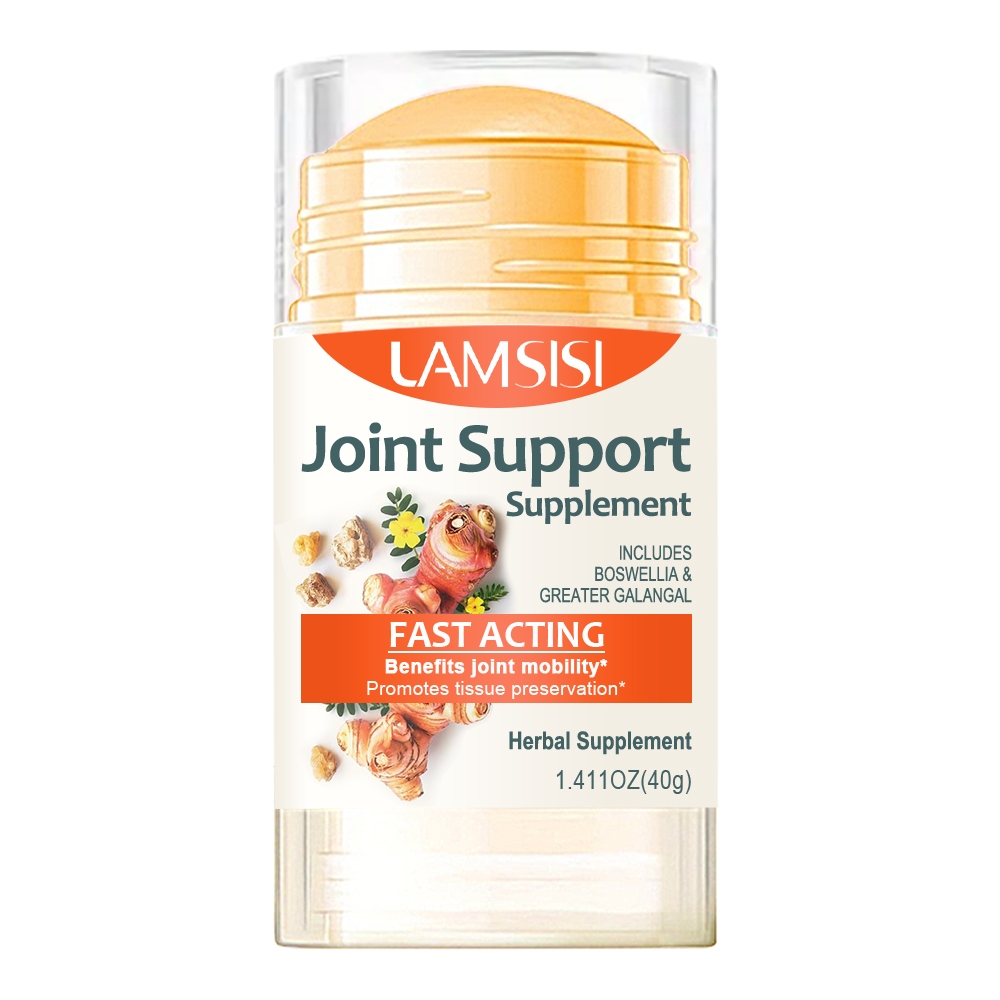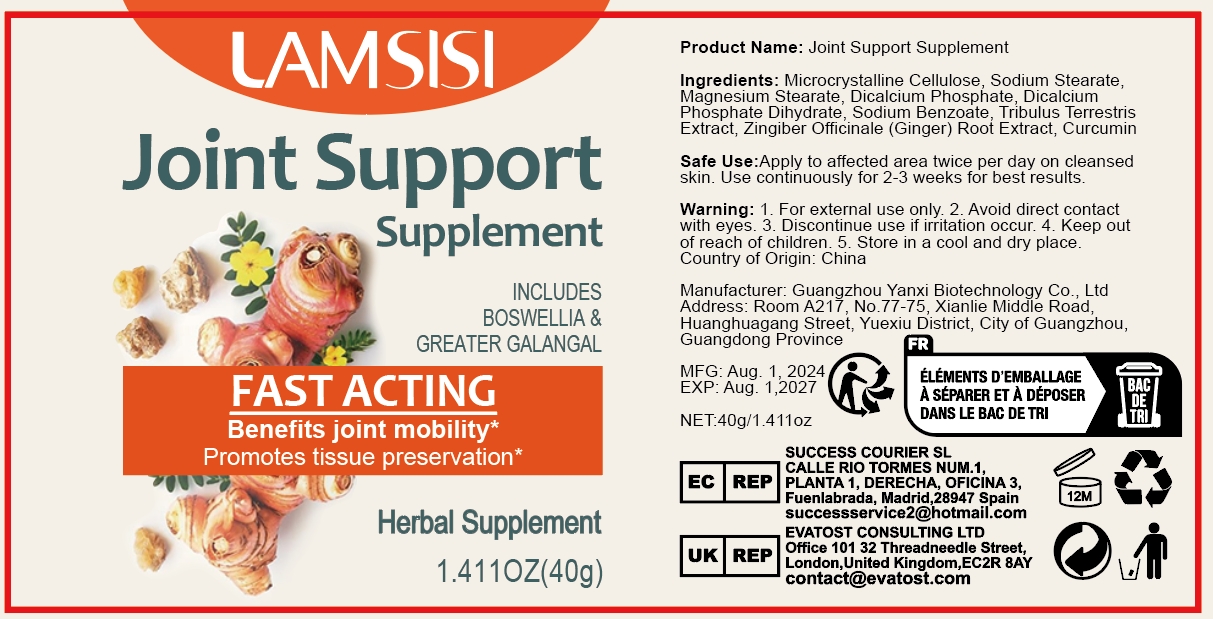 DRUG LABEL: Joint Support Supplement
NDC: 84025-254 | Form: CREAM
Manufacturer: Guangzhou Yanxi Biotechnology Co., Ltd
Category: otc | Type: HUMAN OTC DRUG LABEL
Date: 20241108

ACTIVE INGREDIENTS: ZINGIBER OFFICINALE (GINGER) ROOT EXTRACT 2 mg/40 g; MICROCRYSTALLINE CELLULOSE 3 mg/40 g
INACTIVE INGREDIENTS: WATER

DOSAGE AND ADMINISTRATION

Apply to affected area twice per day on cleansed skin.Use continuously for 2-3 weeks for best results.

WARNINGS

Keep out of children

INACTIVE INGREDIENT

Aqua

INDICATIONS AND USAGE

For daily skin care

Keep out of children

PURPOSE

Promotes tissue preservation